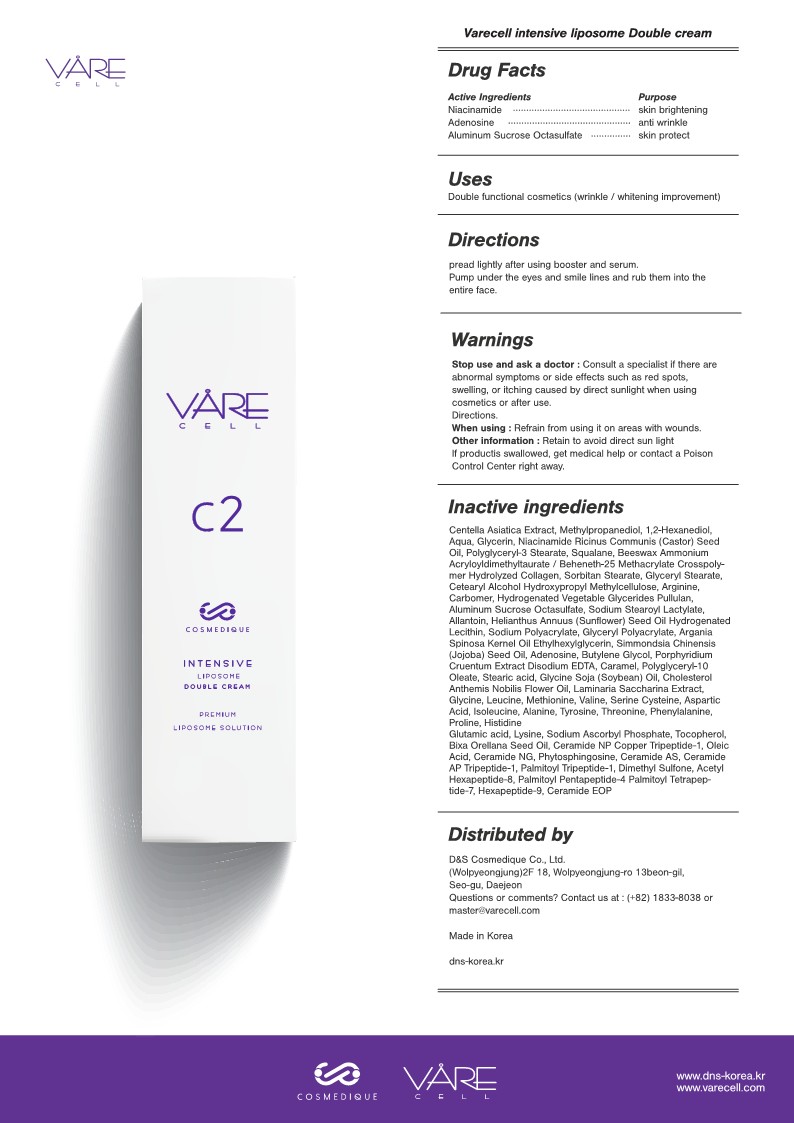 DRUG LABEL: Varecell Intensive Liposome DoubleCream
NDC: 82190-104 | Form: CREAM
Manufacturer: D&S Cosmedique Co.Ltd.
Category: otc | Type: HUMAN OTC DRUG LABEL
Date: 20210907

ACTIVE INGREDIENTS: ADENOSINE 0.04 g/100 mL; NIACINAMIDE 2 g/100 mL; SUCRALFATE 0.18 g/100 mL
INACTIVE INGREDIENTS: GLYCERIN; CASTOR OIL; YELLOW WAX; CARBOMER HOMOPOLYMER, UNSPECIFIED TYPE; CARAMEL; VALINE; STEARIC ACID; SOYBEAN OIL; CHOLESTEROL; SACCHARINA LATISSIMA; GLYCINE; SERINE; ARGININE; ACETYL HEXAPEPTIDE-8; WATER; POLYGLYCERYL-3 STEARATE; ALLANTOIN; HYDROGENATED SOYBEAN LECITHIN; ARGAN OIL; SODIUM ASCORBYL PHOSPHATE; BIXA ORELLANA SEED OIL; PHYTOSPHINGOSINE; CERAMIDE 4; DIMETHYL SULFONE; PALMITOYL PENTAPEPTIDE-4; SQUALANE; SORBITAN MONOSTEARATE; CETOSTEARYL ALCOHOL; ASPARTIC ACID; ISOLEUCINE; TYROSINE; THREONINE; PROLINE; LEUCINE; METHIONINE; HEXAPEPTIDE-9; PHENYLALANINE; LYSINE; PREZATIDE COPPER; CERAMIDE NG; PREZATIDE; PALMITOYL TRIPEPTIDE-1; CERAMIDE 1; HISTIDINE; GLUTAMIC ACID; TOCOPHEROL; CERAMIDE NP; OLEIC ACID; CERAMIDE AP; PALMITOYL TETRAPEPTIDE-7; HYDROGENATED PALM GLYCERIDES; PULLULAN; EDETATE DISODIUM ANHYDROUS; SODIUM STEAROYL LACTYLATE; SUNFLOWER OIL; SODIUM POLYACRYLATE (8000 MW); ETHYLHEXYLGLYCERIN; JOJOBA OIL; POLYGLYCERYL-10 OLEATE; ALANINE; AMMONIUM ACRYLOYLDIMETHYLTAURATE/BEHENETH-25 METHACRYLATE CROSSPOLYMER (52000 MPA.S); CYSTEINE; COLLAGEN ALPHA-1(I) CHAIN BOVINE; GLYCERYL MONOSTEARATE; BUTYLENE GLYCOL; HYPROMELLOSE, UNSPECIFIED

82190-104 Varecell Intensive Liposome Double Cream

Active Ingredients

Niacinamide (2%)
Aluminum Sucrose Octasulfate (0.18%)
Adenosine (0.04%)

Purpose

Prevent wrinkles and brighten skin

Uses

Spread lightly after using booster and serum.

Pump under the eyes and smile lines and rub them into the entire face.

Warnings

Consult a specialist if there are abnormal symptoms or side effects such as red spots, swelling, or itching caused by direct sunlight when using cosmetics or after use.

Warnings

Refrain from using it on areas with wounds.

Other Information

Retain to avoid direct sunlight.

If product is swallowed, get medical help or contact a Poison Control Center right away.

Inactive Ingredients

Centella Asiatica Extract, Methylpropanediol, 1,2-Hexanediol, Aqua, Glycerin, Niacinamide, Ricinus Communis (Castor) Seed Oil, Polyglyceryl-3 Stearate, Squalane, Beeswax, Ammonium Acryloyldimethyltaurate/Beheneth-25 Methacrylate Crosspolymer, Hydrolyzed Collagen, Sorbitan Stearate, Glyceryl Stearate, Cetearyl Alcohol, Hydroxypropyl Methylcellulose, Arginine, Carbomer, Hydrogenated Vegetable Glycerides, Pullulan, Aluminum Sucrose Octasulfate, Sodium Stearoyl Lactylate, Allantoin, Helianthus Annuus (Sunflower) Seed Oil, Hydrogenated Lecithin, Sodium Polyacrylate, Glyceryl Polyacrylate, Argania Spinosa Kernel Oil, Ethylhexylglycerin, Simmondsia Chinensis (Jojoba) Seed Oil, Adenosine, Butylene Glycol, Porphyridium Cruentum Extract, Disodium EDTA, Caramel, Polyglyceryl-10 Oleate, Stearic acid, Glycine Soja (Soybean) Oil, Cholesterol, Anthemis Nobilis Flower Oil, Laminaria Saccharina Extract, Glycine, Leucine, Methionine, Valine, Serine, Cysteine, Aspartic Acid, Isoleucine, Alanine, Tyrosine, Threonine, Phenylalanine, Proline, Histidine, Glutamic acid, Lysine, Sodium Ascorbyl Phosphate, Tocopherol, Bixa Orellana Seed Oil, Ceramide NP, Copper Tripeptide-1, Oleic Acid, Ceramide NG, Phytosphingosine, Ceramide AS, Ceramide AP, Tripeptide-1, Palmitoyl Tripeptide-1, Dimethyl Sulfone, Acetyl Hexapeptide-8, Palmitoyl Pentapeptide-4, Palmitoyl Tetrapeptide-7, Hexapeptide-9, Ceramide EOP

Keep out of reach of children

Directions

pread lightly after using booster and serum
Pump under the eyes and smile lines and rub them into the entire face.